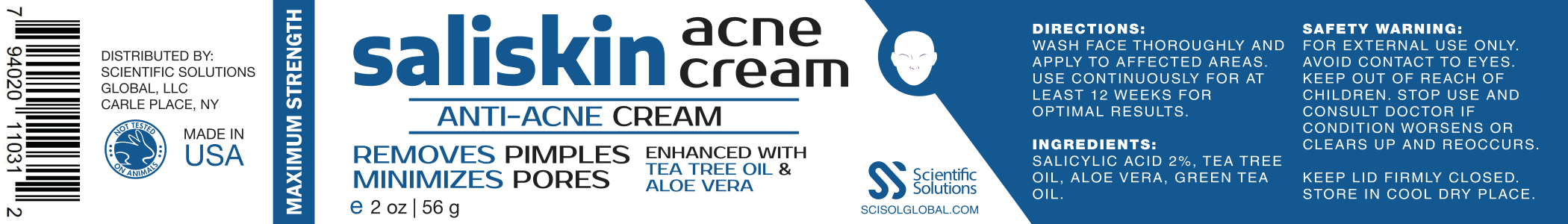 DRUG LABEL: SaliSkin
NDC: 81376-500 | Form: CREAM
Manufacturer: SSG Ventures Inc
Category: otc | Type: HUMAN OTC DRUG LABEL
Date: 20210407

ACTIVE INGREDIENTS: SALICYLIC ACID 2 g/100 g
INACTIVE INGREDIENTS: TEA TREE OIL; GREEN TEA LEAF; ALOE VERA LEAF POLYSACCHARIDES

Saliskin

PACKAGE LABEL

ACTIVE INGREDIENT

SALICYLIC ACID, TEA TREE OIL

INACTIVE INGREDIENT

MEDIDERM CREAM, GREEN TEA EXTRACT, ALOE VERA, EMULTHIX

DOSAGE AND ADMINISTRATION

WASH FACE THOROUGHLY AND APPLY TO AFFECTED AREAS. USE CONTINUOUSLY FOR AT LEAST 12 WEEKS FOR OPTIMAL RESULTS

WARNINGS

FOR EXTERNAL USE ONLY.

AVOID CONTACT TO EYES.

KEEP OUT OF REACH OF CHILDREN.

STOP USE AND CONSULT DOCTOR IF CONDITION WORSENS OR CLEARS UP AND REOOCCURS.

PURPOSE

REMOVES PIMPLES

MINIMIZES PORES

ENHANCED WITH TEA TREE OIL AND ALOE VERA

KEEP OUT OF REACH FO CHILDREN

INDICATIONS AND USAGE

USE CONTINUOUSLY FOR AT LEAST 12 WEEKS FOR OPTIMAL RESULTS